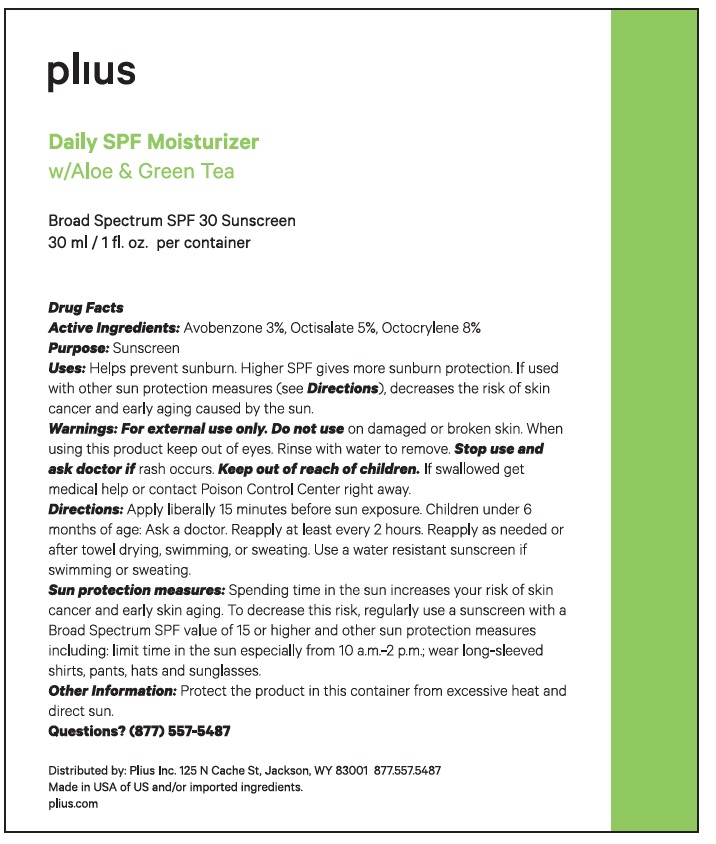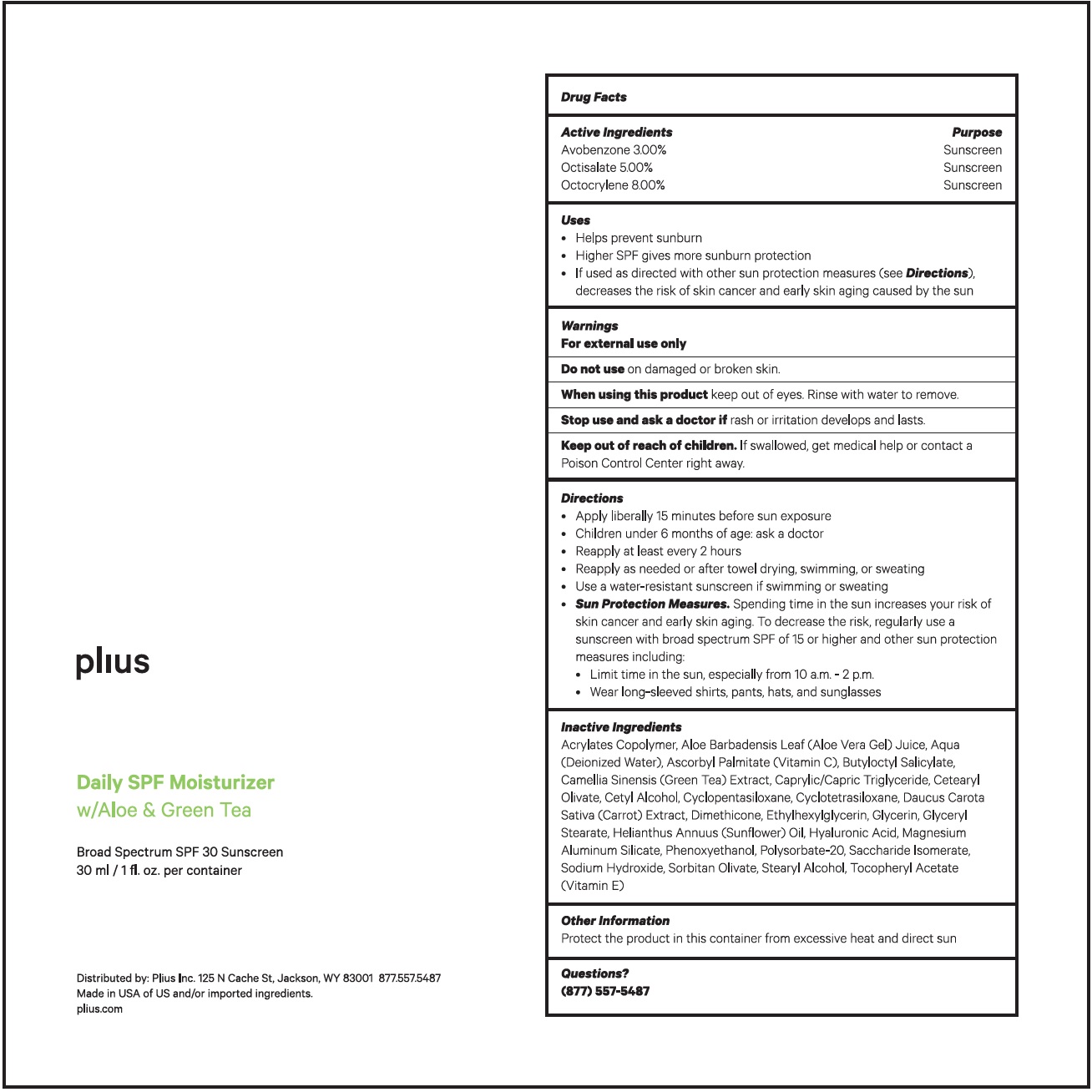 DRUG LABEL: Plius Daily SPF Moisturizer SPF 30
NDC: 80573-089 | Form: CREAM
Manufacturer: PLIUS, Inc
Category: otc | Type: HUMAN OTC DRUG LABEL
Date: 20260119

ACTIVE INGREDIENTS: AVOBENZONE 30 mg/1 mL; OCTISALATE 50 mg/1 mL; OCTOCRYLENE 80 mg/1 mL
INACTIVE INGREDIENTS: BUTYL ACRYLATE/METHYL METHACRYLATE/METHACRYLIC ACID COPOLYMER (18000 MW); ALOE VERA LEAF; WATER; ASCORBYL PALMITATE; BUTYLOCTYL SALICYLATE; GREEN TEA LEAF; MEDIUM-CHAIN TRIGLYCERIDES; CETEARYL OLIVATE; CETYL ALCOHOL; CYCLOMETHICONE 5; CYCLOMETHICONE 4; CARROT; DIMETHICONE; ETHYLHEXYLGLYCERIN; GLYCERIN; GLYCERYL MONOSTEARATE; SUNFLOWER OIL; HYALURONIC ACID; MAGNESIUM ALUMINUM SILICATE; PHENOXYETHANOL; POLYSORBATE 20; SACCHARIDE ISOMERATE; SODIUM HYDROXIDE; SORBITAN OLIVATE; STEARYL ALCOHOL; .ALPHA.-TOCOPHEROL ACETATE

Plius Daily SPF Moisturizer SPF-30

Active Ingredients

Avobenzone 3.00%

Octisalate 5.00%

Octocrylene 8.00%

Purpose

Sunscreen

Uses

- Helps prevent sunburn
- Higher SPF gives more sunburn protection
- If used as directed with other sun protection measures (see) decreases the risk of skin cancer and early skin aging caused by the sun Directions

Warnings

For external use only

Do not use

on damaged or broken skin.

When using this product

keep out of eyes. Rinse with water to remove.

Stop use and ask a doctor if

rash or irritation develops and lasts.

Keep out of reach of children.

If swallowed, get medical help or contact a Poison Control Center right away.

Directions

- Apply liberally 15 minutes before sun exposure
- Children under 6 months of age: ask a doctor
- Reapply at least every 2 hours
- Reapply as needed or after towel drying, swimming, or sweating
- Use a water-resistant sunscreen if swimming or sweating
- Spending time in the sun increases your risk of skin cancer and early skin aging. To decrease the risk, regularly use a sunscreen with broad spectrum SPF of 15 or higher and other sun protection measures including: Sun Protection Measures.
- Limit time in the sun, especially from 10 am. - 2 p.m.
- Wear long-sleeved shirts, pants, hats, and sunglasses

Inactive ingredients

Acrylates Copolymer, Aloe Barbadensis Leaf (Aloe Vera Ge) Juice, Aqua(Deionized Water), Ascorbyl Palmitate (Vitamin C), Butyloctyl Salicylate Camellia Sinensis (Green Tea) Extract, Caprylic/Capric Triglyceride, Cetearyl Olivate, Cetyl Alcohol, Cyclopentasiloxane, Cyclotetrasiloxane, Daucus Carota Sativa (Carrot) Extract, Dimethicone, Ethylhexylglycerin, Glycerin, Glyceryl Stearate, Helianthus Annuus (Sunflower) Oil, Hyaluronic Acid, Magnesium Aluminum Silicate, Phenoxyethanol, Polysorbate-20, Saccharide Isomerate, Sodium Hydroxide, Sorbitan Olivate, Stearyl Alcohol, Tocopheryl Acetate (Vitamin E)

Other Information:

Protect the product in this container from excessive heat and direct sun.

Questions?

(877)557-5487